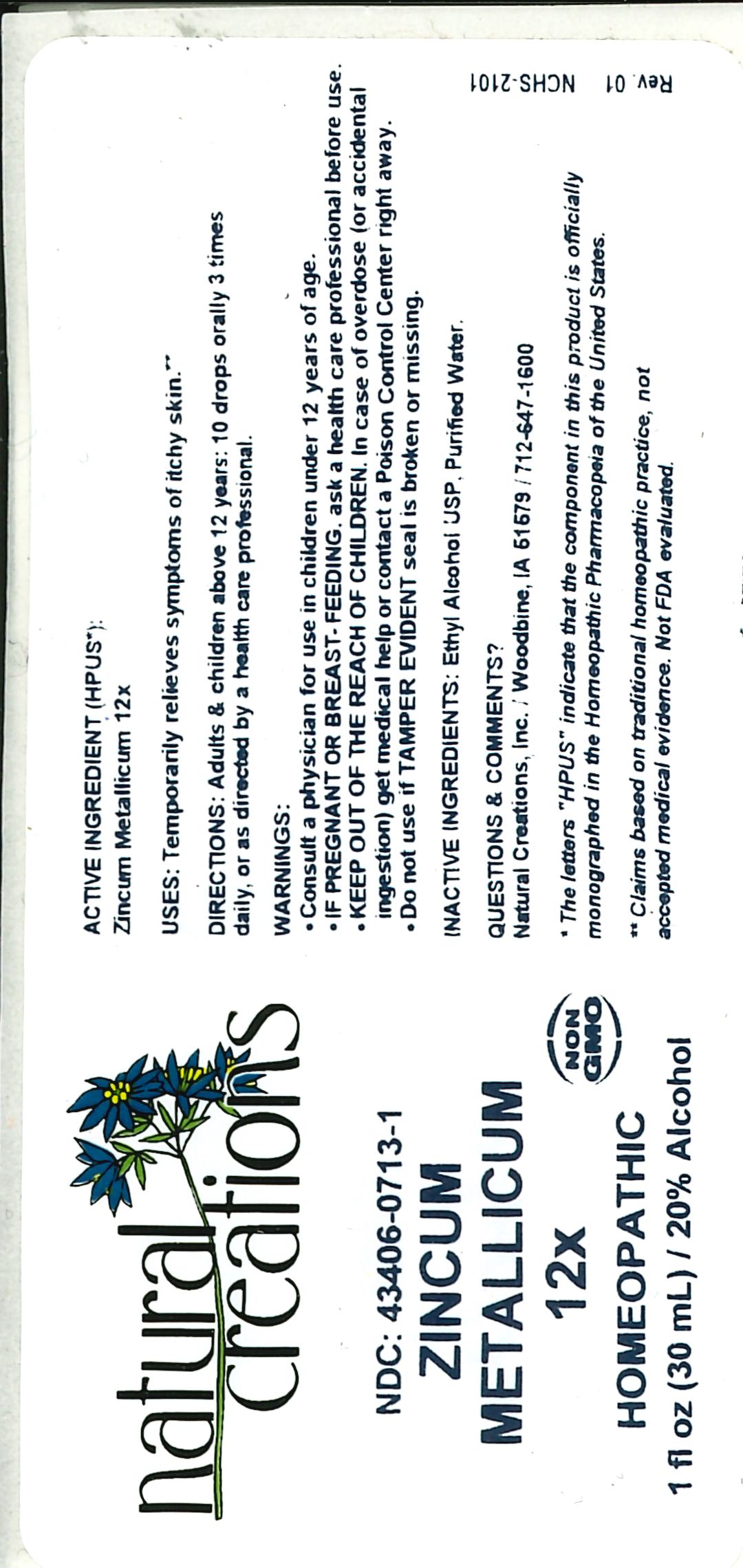 DRUG LABEL: Zincum Metallicum 12X
NDC: 43406-0713 | Form: LIQUID
Manufacturer: Natural Creations, Inc
Category: homeopathic | Type: HUMAN OTC DRUG LABEL
Date: 20251218

ACTIVE INGREDIENTS: ZINC 12 [hp_X]/1 mL
INACTIVE INGREDIENTS: ALCOHOL; WATER

Zincum Metallicum 12X

ACTIVE INGREDIENTS (*HPUS) - Zincum Metallicum 12X

INDICATIONS AND USAGE

USES: Temporarily relieves symptoms of itchy skin.**

PURPOSE

USES: Temporarily relieves symptoms of itchy skin.**

DOSAGE AND ADMINISTRATION

DIRECTIONS: Adults & children above 12 years: 10 drops orally 3 times daily, or as directed by a health care professional.

KEEP OUT OF REACH OF CHILDREN

KEEP OUT OF THE REACH OF CHILDREN. In case of overdose (or accidental ingestion) get medical help or contact a Poison Control Center right away.

WARNINGS:

- Consult a physician for use in children under 12 years of age.
- IF PREGNANT OR BREAST-FEEDING, ask a health care professional before use.
- KEEP OUT OF THE REACH OF CHILDREN. In case of overdose (or accidental ingestion) get medical help or contact a Poison Control Center right away.
- Do not use if TAMPER EVIDENT seal is broken or missing.

INACTIVE INGREDIENTS: Ethyl Alcohol USP, Purified Water.

QUESTIONS & COMMENTS?

Natural Creations, Inc. / Woodbine, IA 51579 / 712-647-1600

REFERENCES

*The letters "HPUS" indicate the components in this product are officially monographed in the Homeopathic Pharmacopeia of the United States.

**Claims based on traditional homeopathic practice, not accepted medical evidence. Not FDA evaluated.

PACKAGE LABEL

NDC:43406-0713-1

Zincum Metallicum 12X

HOMEOPATHIC

1 fl oz (30mL) / 20% Alcohol